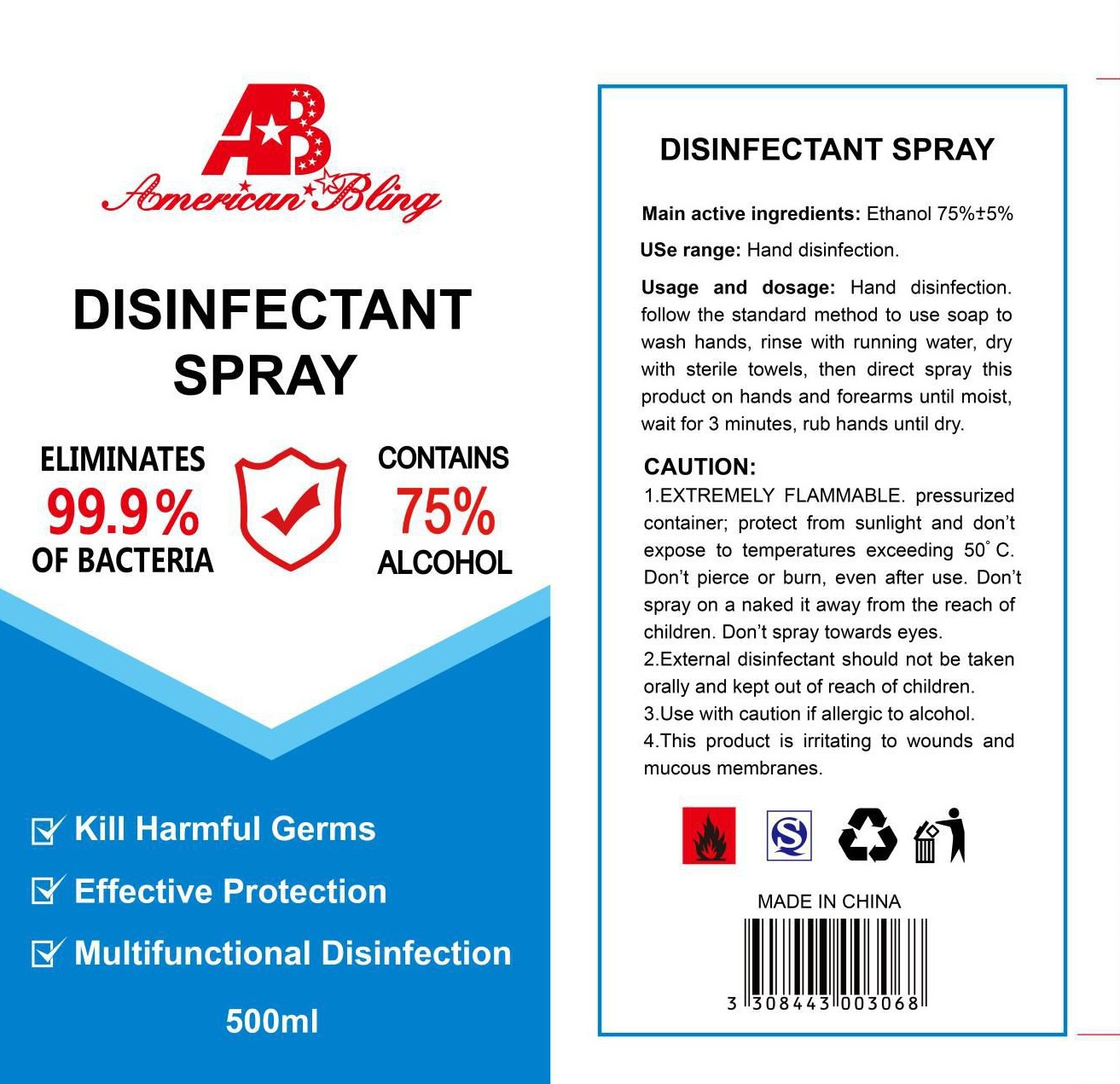 DRUG LABEL: DISINFECTANTSPRAY
NDC: 75556-501 | Form: LIQUID
Manufacturer: ZHEJIANG SHUNAN INDUSTRY&TRADE CO.,LTD
Category: otc | Type: HUMAN OTC DRUG LABEL
Date: 20200817

ACTIVE INGREDIENTS: ALCOHOL 375 mL/500 mL
INACTIVE INGREDIENTS: WATER

75556-501 500ml 75% spray

Active Ingredient(s)

Alcohol 75% v/v,Antiseptic

Purpose

Antiseptic, Disinfectant spray.

Use

USE range:Hand disinfection.

follow the standard method to use soap to wash hands, rinse with running water, dry with sterile towels, then direct spray this product on hands and forearms until moist, wait for 3 minutes, rub hands until dry.

Warnings

1.EXTREMELY FLAMMABLE. pressurized container; protect from sunlight and don't expose to temperatures exceeding 50℃. Don't pierce or burn, even after use. Don't spray on a naked it away from the reach of children. Don't spray towards eyes.

2.External disinfectant should not be taken orally and kept out of reach of children.

3.Use with caution if allergic to alcohol.

4.This product is irritating to wounds and mucous membranes.

Directions

Hand disinfection.

follow the standard method to use soap to wash hands, rinse with running water, dry with sterile towels, then direct spray this product on hands and forearms until moist, wait for 3 minutes, rub hands until dry.

Inactive ingredients

Water.

DISINFECTANT SPRAY

ELIMINATES 99.9% OF BACTERIA

CONTAINS 75% ALCOHOL

- KILL HARMFUL GERMS
- EFFECTIVE PROTECTION
- MULTIFUNCTIONAL DISINFECTION

500ml

MADE IN CHINA

STORAGE AND HANDLING

EXTREMELY FLAMMABLE. pressurized container; protect from sunlight and don't expose to temperatures exceeding 50℃. Don't pierce or burn, even after use. Don't spray on a naked it away from the reach of children. Don't spray towards eyes.

KEEP OUT OF REACH OF CHILDREN

- External disinfectant should not be taken orally and kept out of reach of children.

Package Label - Principal Display Panel

500 mL in 1 bottle NDC: 75556-501-01